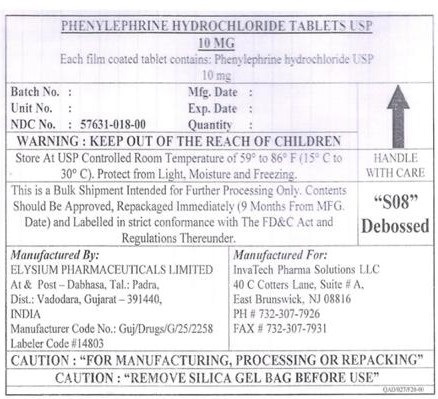 DRUG LABEL: Phenylephrine Hydrochloride
NDC: 57631-018 | Form: TABLET
Manufacturer: InvaTech Pharma Solutions LLC
Category: otc | Type: HUMAN OTC DRUG LABEL
Date: 20251001

ACTIVE INGREDIENTS: PHENYLEPHRINE HYDROCHLORIDE 10 mg/1 1
INACTIVE INGREDIENTS: MAGNESIUM STEARATE; TALC; POLYETHYLENE GLYCOL 400; TITANIUM DIOXIDE; POLYVINYL ALCOHOL, UNSPECIFIED; CALCIUM PHOSPHATE; MICROCRYSTALLINE CELLULOSE; CROSCARMELLOSE SODIUM; SILICON DIOXIDE

Phenylephrine Hydrochloride